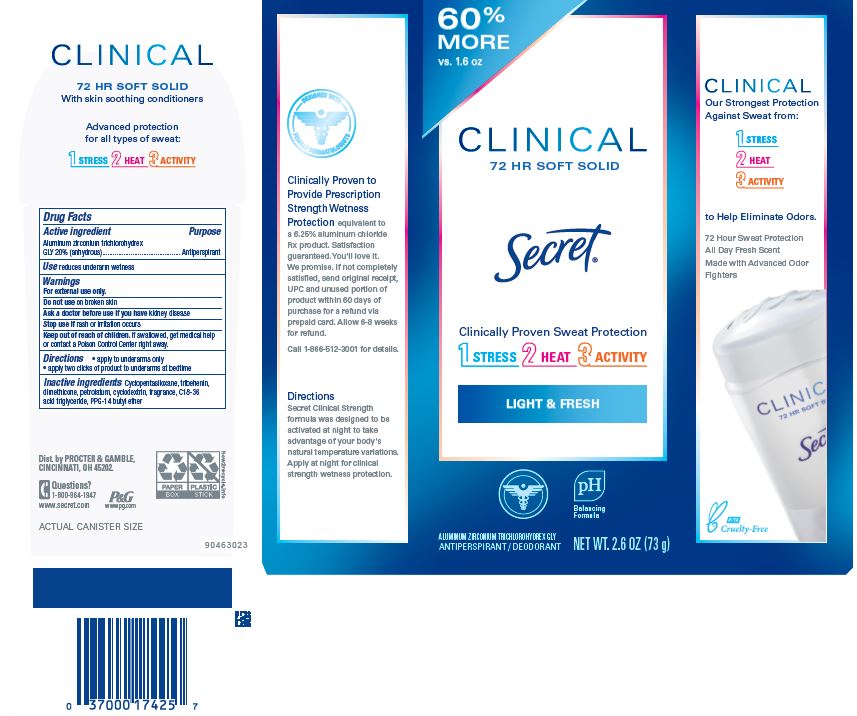 DRUG LABEL: Secret Clinical Light and Fresh Soft
NDC: 69423-711 | Form: CREAM
Manufacturer: The Procter & Gamble Manufacturing Company
Category: otc | Type: HUMAN OTC DRUG LABEL
Date: 20251231

ACTIVE INGREDIENTS: ALUMINUM ZIRCONIUM TRICHLOROHYDREX GLY 20 g/100 g
INACTIVE INGREDIENTS: CYCLODEXTRINS; C18-36 ACID TRIGLYCERIDE; CYCLOPENTASILOXANE; DIMETHICONE; PETROLATUM; TRIBEHENIN; PPG-14 BUTYL ETHER

Secret® Clinical Light and Fresh Soft Solid

Drug Facts

Active ingredient

Aluminum zirconium trichlorohydrex Gly 20% (anhydrous)

Purpose

Antiperspirant

Use

- reduces underarm wetness

Warnings

For external use only.

Do not use on broken skin

Ask a doctor before use if you have kidney disease

Stop use if rash or irritation occurs

Keep out of reach of children. If swallowed, get medical help or contact a Poison Control Center right away.

Directions

- apply to underarms only
- apply two clicks of product to underarms at bedtime

Inactive ingredients

cyclopentasiloxane, tribehenin, dimethicone, petrolatum, cyclodextrin, fragrance, C18-36 acid triglyceride, PPG-14 butyl ether

Questions?

1-800-964-1947

Dist. by PROCTER & GAMBLE,
CINCINNATI, OH 45202.

PRINCIPAL DISPLAY PANEL -73 g Cylinder Carton

Secret®

CLINICAL

72 HR Soft Solid

LIGHT AND FRESH

ALUMINUM ZIRCONIUM TRICHLOROHYDREX GLY

ANTIPERSPIRANT/DEODORANT

NET WT. 2.6 OZ. (73 g)